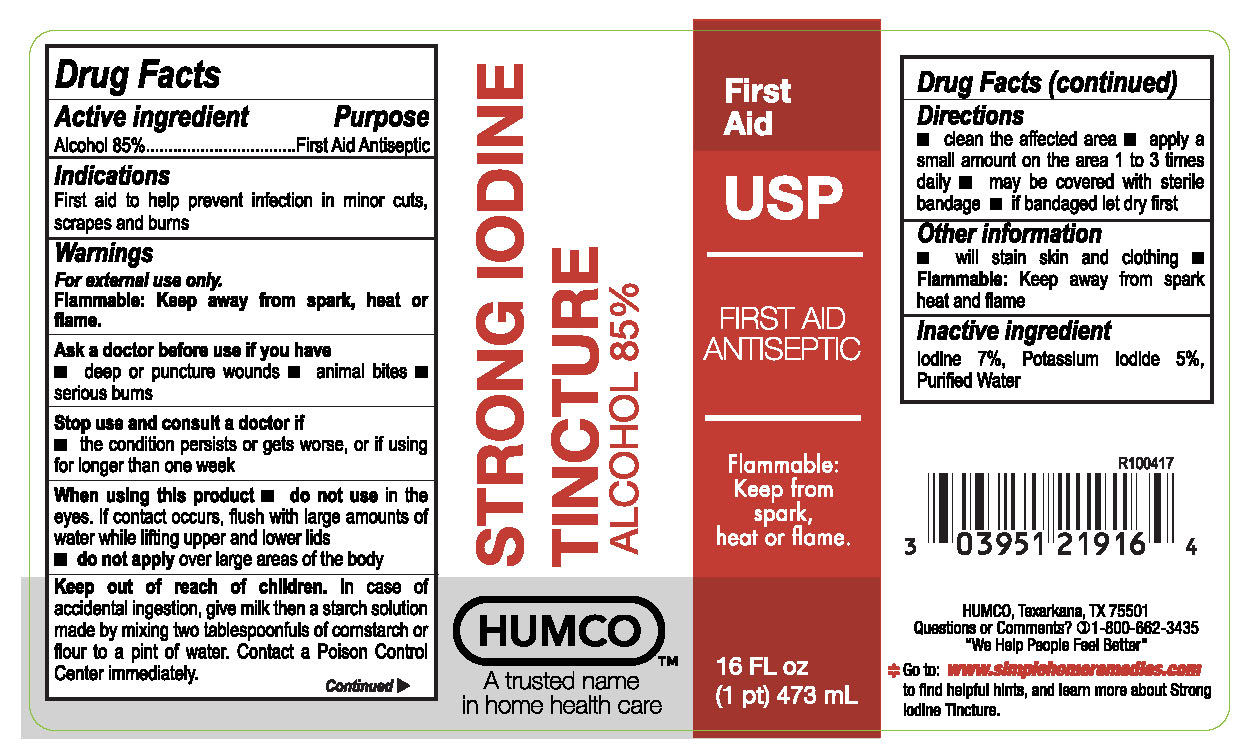 DRUG LABEL: Strong Iodine Tincture
NDC: 0395-1220 | Form: LIQUID
Manufacturer: Humo Holding Group, Inc.
Category: otc | Type: HUMAN OTC DRUG LABEL
Date: 20171109

ACTIVE INGREDIENTS: ALCOHOL 850 mg/1 mL
INACTIVE INGREDIENTS: WATER; IODINE; POTASSIUM IODIDE

Humco Strong Iodine Tincture

Drug Facts

Active Ingredient

Alcohol 85%

Purpose

Antiseptic

Uses

To prevent infection in mior cuts, scrapes, and burns.

Warnings

For external use only

Ask a doctor if you have:

deep or puncture wounds

animal bites

serious burns.

Stop use and consult a doctor if:

The condition persists or gets worse, or if using for longer than once a week.

When using this product:

Do not use in the eyes. If contact occurs, flush with large amounts of water lifting upper and lower lids.

do not apply over large areas of the body.

Keep out of reach of children

In case of accidental ingestion, give milk then a starch solution made by mixing two tablespoonfuls of cornstarch or flour to a pint of water. contact a Poison Control Center immediately.

Directions

Clean affacted area

Apply a small amount on the area 1 to 3 times daily.

May be covered with sterile bandage.

If bandaged, let it dry first.

Inactive Ingredient

Iodine 7%, Potassium Iodide 5%, Purified water